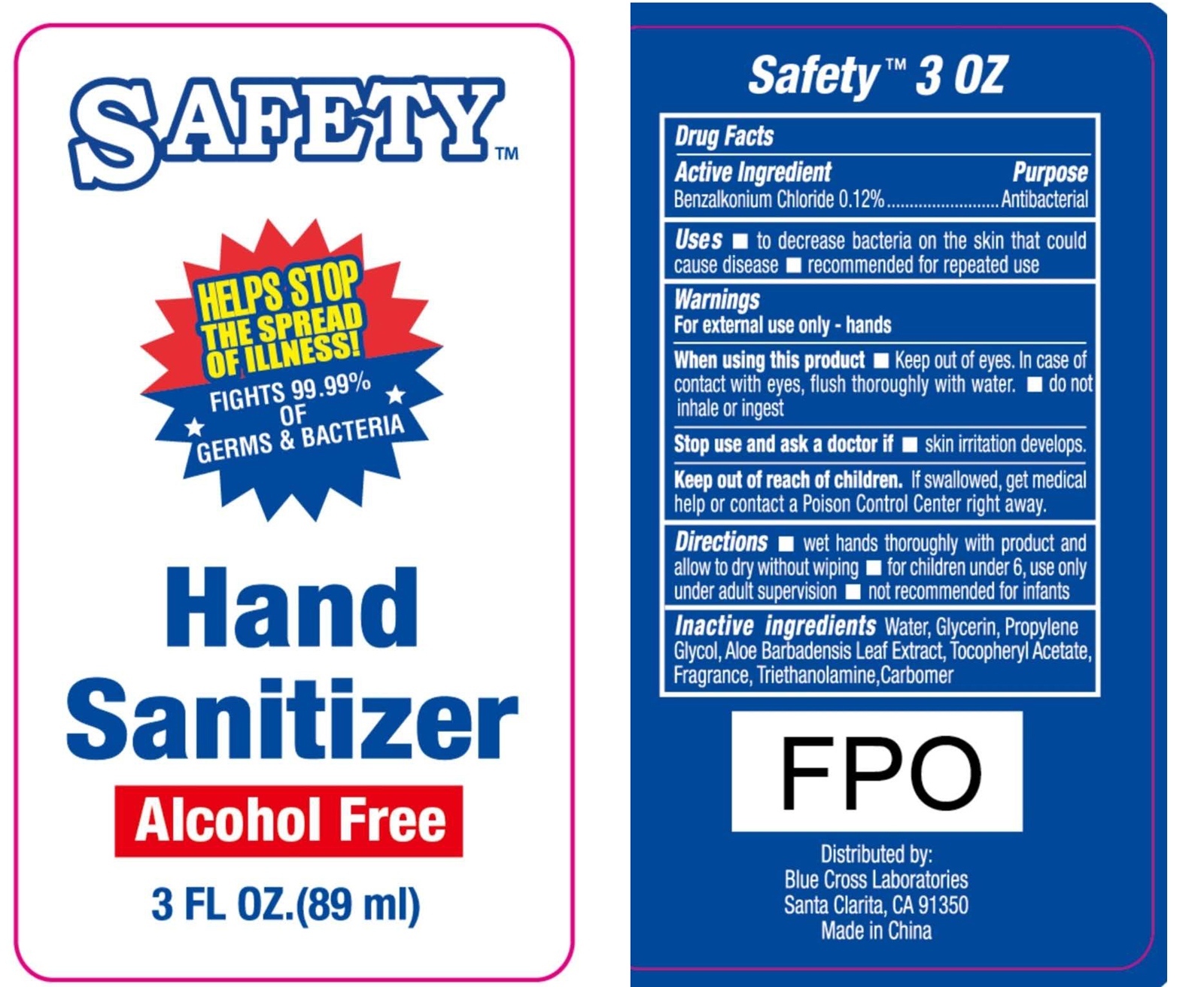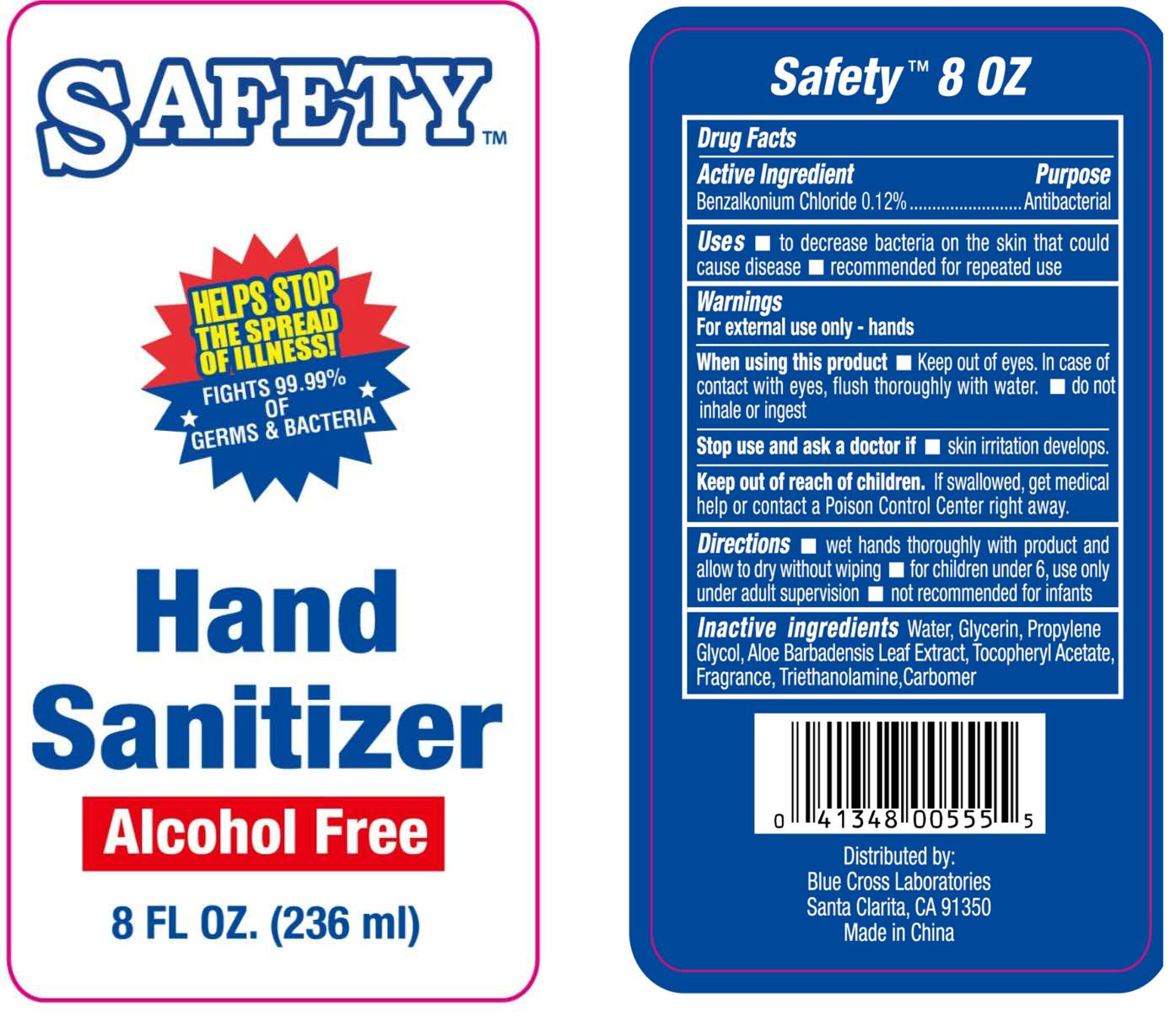 DRUG LABEL: Hand Sanitizer
NDC: 22431-150 | Form: GEL
Manufacturer: BLUE CROSS LABORATORIES
Category: otc | Type: HUMAN OTC DRUG LABEL
Date: 20200806

ACTIVE INGREDIENTS: BENZALKONIUM CHLORIDE 0.12 g/100 mL
INACTIVE INGREDIENTS: CARBOMER HOMOPOLYMER, UNSPECIFIED TYPE; GLYCERIN; ALPHA-TOCOPHEROL ACETATE; WATER; TROLAMINE; PROPYLENE GLYCOL; ALOE VERA LEAF

Hand sanitizer

Active Ingredient(s)

Benzalkonium Chloride 0.12%. Purpose: Antibacterial

Purpose

Antibacterial, Hand Sanitizer

Use

- to decrease bacteria on the skin that could cause disease
- recommended for repeated use

Warnings

For external use only - hands

WHEN USING

- Keep out of eyes. In case of contact with eyes, flush thoroughly with water.
- do not inhale or ingest

Stop use and ask a doctor

if skin irritation develops.

Keep out of reach of children.

If swallowed, get medical help or contact a Poison Control Center right away.

Directions

- wet hands thoroughly with product and allow to dry without wiping
- for children under 6, use only under adult supervision
- not recommended for infants

Inactive ingredients

Water, glycerin, propylene glycol, Aloe barbadensis leaf extract, tocopheryl acetate, fragrance, triethanolamine, carbomer

Package Label - Principal Display Panel

89 mL NDC: 22431-150-01

236 mL NDC: 22431-150-02